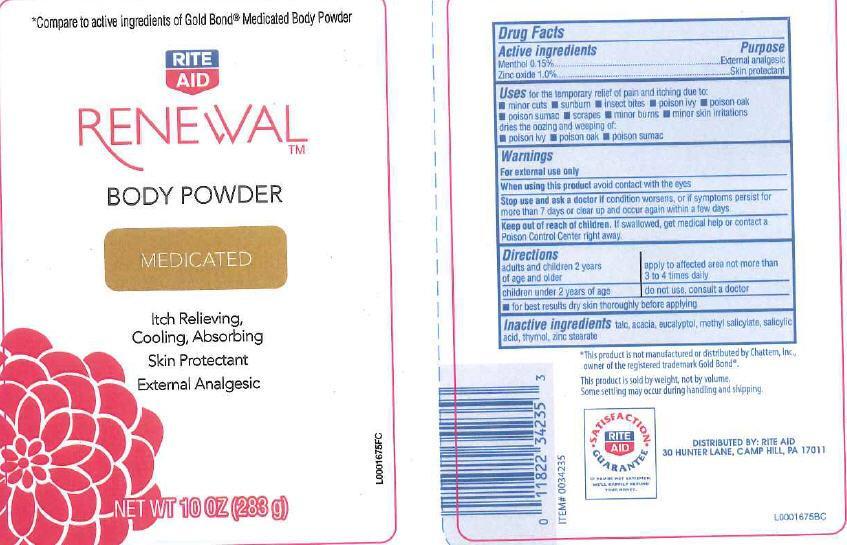 DRUG LABEL: body
NDC: 11822-0551 | Form: POWDER
Manufacturer: Rite Aid
Category: otc | Type: HUMAN OTC DRUG LABEL
Date: 20130121

ACTIVE INGREDIENTS: MENTHOL 1.5 mg/1 g; ZINC OXIDE 10 mg/1 g
INACTIVE INGREDIENTS: TALC; ACACIA; EUCALYPTOL; METHYL SALICYLATE; SALICYLIC ACID; THYMOL; ZINC STEARATE

Drug facts

Active ingredient

Menthol 0.15%

Zinc Oxide 1.0%

Purpose

External analgesic

Skin protectant

Use

Uses for temporary relief of pan and itching due to

- minor cuts
- sun burn
- insect bites
- poison ivy
- poison oak
- poison sumac
- scrapes
- minor burns
- minor skin irritations

dries the oozing and weeping of:

- poison ivy
- poison oak
- poison sumac

Warnings

For external use only

When using this product avoid contact with the eyes

Stop use and ask a doctor if condition worses, or if symptoms persist for more than 7 days or clear up and occur again within a few days.

Keep out of reach of children. If swallowed, get medical help or contact a Poison Control Center right away.

Directions

adults and children 2 years of age and older - apply to affected area not more than 3 to 4 times daily

children under 2 years of age - do not use, consult a doctor

- for best results dry skin thoroughly before applying

Inactive ingredients

Inactive ingredients talc, acacia, eucalyptol, methyl salicylate, salicylic acid, thymol, zinc stearate

Disclaimer

This product is not manufactured or distributed by Chattem, Inc., owner of the registered trademark Gold Bond.

This product is sold by weight, not by volume. Some settling may occur during handling and shipping.

advese reactions

DISTRIBUTED BY: RITE AID

30 HUNTER LANE, CAMP HILL, PA 17011

Principal Display Panel

Compare to active ingredients of Gold Bond Medicated Body Powder

RITE

AID

RENEWAL

BODY POWDER

MEDICATED

Itch Relieving,

Cooling, Absorbing

Skin Protectant

External Analgesic

NET WT 10 OZ (283 g)